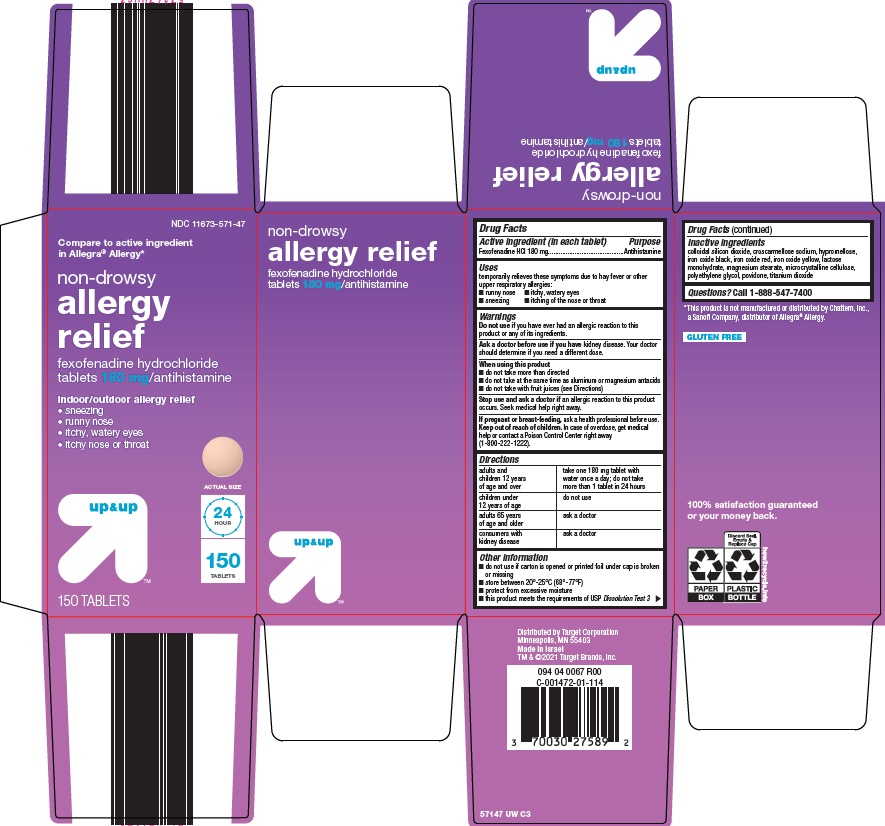 DRUG LABEL: up and up allergy relief
NDC: 11673-571 | Form: TABLET, FILM COATED
Manufacturer: Target Corporation
Category: otc | Type: HUMAN OTC DRUG LABEL
Date: 20220525

ACTIVE INGREDIENTS: FEXOFENADINE HYDROCHLORIDE 180 mg/1 1
INACTIVE INGREDIENTS: SILICON DIOXIDE; CROSCARMELLOSE SODIUM; HYPROMELLOSE, UNSPECIFIED; FERROSOFERRIC OXIDE; FERRIC OXIDE RED; FERRIC OXIDE YELLOW; LACTOSE MONOHYDRATE; MAGNESIUM STEARATE; MICROCRYSTALLINE CELLULOSE; POLYETHYLENE GLYCOL, UNSPECIFIED; POVIDONE, UNSPECIFIED; TITANIUM DIOXIDE

Target Corporation Allergy Relief Drug Facts

Active ingredient (in each tablet)

Fexofenadine HCl 180 mg

Purpose

Antihistamine

Uses

temporarily relieves these symptoms due to hay fever or other upper respiratory allergies:

- runny nose
- itchy, watery eye
- sneezing
- itching of the nose or throat

Warnings

Do not use

if you have ever had an allergic reaction to this product or any of its ingredients.

Ask a doctor before use if you have

kidney disease. Your doctor should determine if you need a different dose.

When using this product

- do not take more than directed
- do not take at the same time as aluminum or magnesium antacids
- do not take with fruit juices (see Directions)

Stop use and ask a doctor if

an allergic reaction to this product occurs. Seek medical help right away.

If pregnant or breast-feeding,

ask a health professional before use.

Keep out of reach of children.

In case of overdose, get medical help or contact a Poison Control Center right away (1-800-222-1222).

Directions

adults and children 12 years of age and over | take one 180 mg tablet with water once a day; do not take more than 1 tablet in 24 hours
children under 12 years of age | do not use
adults 65 years of age and older | ask a doctor
consumers with kidney disease | ask a doctor

Other information

- do not use if carton is opened or printed foil under cap is broken or missing
- store between 20°-25°C (68°-77°F)
- protect from excessive moisture
- this product meets the requirements of USP Dissolution Test 3

Inactive ingredients

colloidal silicon dioxide, croscarmellose sodium, hypromellose, iron oxide black, iron oxide red, iron oxide yellow, lactose monohydrate, magnesium stearate, microcrystalline cellulose, polyethylene glycol, povidone, titanium dioxide

Questions?

Call 1-888-547-7400

Package/Label Principal Display Panel

Compare to active ingredient in Allegra® Allergy

non-drowsy allergy relief

fexofenadine hydrochloride tablets 180 mg/antihistamine

indoor/outdoor allergy relief

● sneezing

● runny nose

● itchy, watery eyes

● itchy nose or throat

ACTUAL SIZE

24 HOUR

150 TABLETS

150 TABLETS